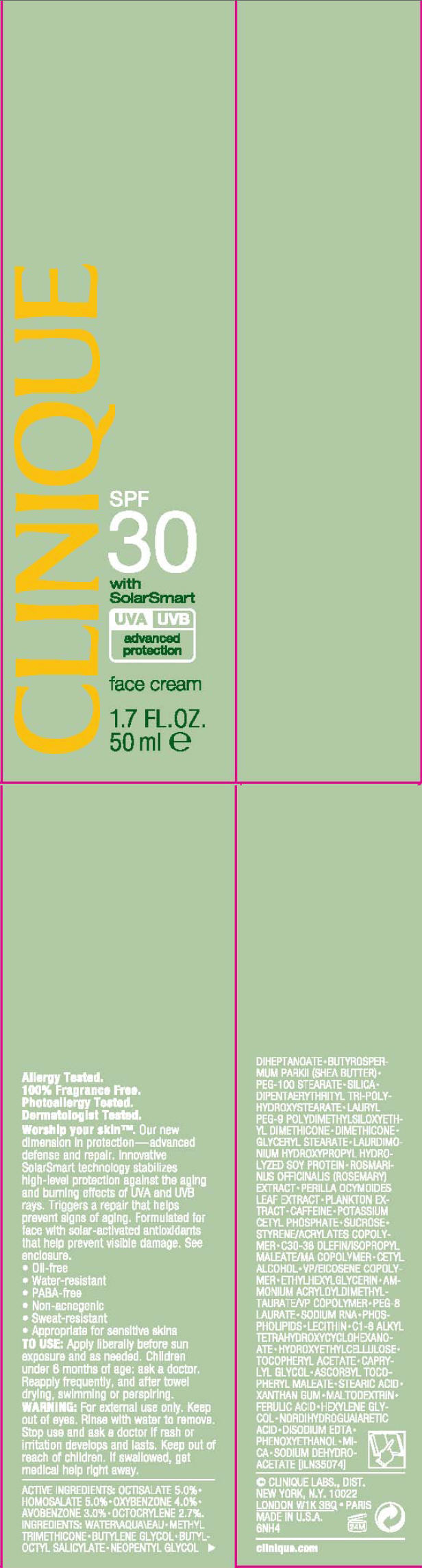 DRUG LABEL: CLINIQUE 
NDC: 49527-716 | Form: CREAM
Manufacturer: CLINIQUE LABORATORIES INC.
Category: otc | Type: HUMAN OTC DRUG LABEL
Date: 20111015

ACTIVE INGREDIENTS: octisalate 5 mL/100 mL; homosalate 5 mL/100 mL; oxybenzone 4 mL/100 mL; avobenzone 3 mL/100 mL; octocrylene 2.7 mL/100 mL
INACTIVE INGREDIENTS: water; methyl trimethicone; butylene glycol; butyloctyl salicylate; neopentyl glycol diheptanoate; shea butter; peg-100 stearate; silicon dioxide; dimethicone; glyceryl monostearate; rosemary; perilla frutescens leaf; caffeine; potassium cetyl phosphate; sucrose; cetyl alcohol; ethylhexylglycerin; peg-8 laurate; alpha-tocopherol acetate; caprylyl glycol; stearic acid; xanthan gum; maltodextrin; ferulic acid; hexylene glycol; masoprocol; edetate disodium; phenoxyethanol; mica; sodium dehydroacetate

CLINIQUE
SPF
30
with
SolarSmart

TO USE

Apply liberally before sun exposure and as needed. Children under 6 months of age: ask a doctor. Reapply frequently, and after towel drying, swimming or perspiring.

WARNING

WHEN USING

For external use only. Keep out of eyes. Rinse with water to remove.

Stop use and ask a doctor if rash or irritation develops and lasts.

Keep out of reach of children. If swallowed, get medical help right away.

ACTIVE INGREDIENTS

OCTISALATE 5.0% • HOMOSALATE 5.0% • OXYBENZONE 4.0% • AVOBENZONE 3.0% • OCTOCRYLENE 2.7%.

INGREDIENTS

WATER • METHYL TRIMETHICONE • BUTYLENE GLYCOL • BUTYLOCTYL SALICYLATE • NEOPENTYL GLYCOL DIHEPTANOATE • BUTYROSPERMUM PARKII (SHEA BUTTER) • PEG-100 STEARATE • SILICA • DIPENTAERYTHRITYL TRI-POLYHYDROXYSTEARATE • LAURYL PEG-9 POLYDIMETHYLSILOXYETHYL DIMETHICONE • DIMETHICONE • GLYCERYL STEARATE • LAURDIMONIUM HYDROXYPROPYL HYDROLYZED SOY PROTEIN • ROSMARINUS OFFICINALIS (ROSEMARY) EXTRACT • PERILLA OCYMOIDES LEAF EXTRACT • PLANKTON EXTRACT • CAFFEINE • POTASSIUM CETYL PHOSPHATE • SUCROSE • STYRENE/ACRYLATES COPOLYMER • C30-38 OLEFIN/ISOPROPYL MALEATE/MA COPOLYMER • CETYL ALCOHOL • VP/EICOSENE COPOLYMER • ETHYLHEXYLGLYCERIN • AMMONIUM ACRYLOYLDIMETHYLTAURATE/VP COPOLYMER • PEG-8 LAURATE • SODIUM RNA • PHOSPHOLIPIDS • LECITHIN • C1-8 ALKYL TETRAHYDROXYCYCLOHEXANOATE • HYDROXYETHYLCELLULOSE • TOCOPHERYL ACETATE • CAPRYLYL GLYCOL • ASCORBYL TOCOPHERYL MALEATE • STEARIC ACID • XANTHAN GUM • MALTODEXTRIN • FERULIC ACID • HEXYLENE GLYCOL • NORDIHYDROGUAIARETIC ACID • DISODIUM EDTA • PHENOXYETHANOL • MICA • SODIUM DEHYDROACETATE [ILN35074]

CLINIQUE LABS., DIST.
NEW YORK, N.Y. 10022

PRINCIPAL DISPLAY PANEL - 50 ml Carton

CLINIQUE

SPF
30
with
SolarSmart

UVA UVB
advanced
protection

face cream

1.7 FL. OZ.
50 ml e